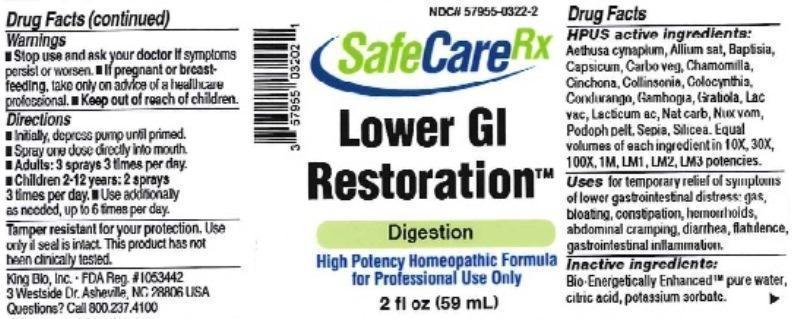 DRUG LABEL: Lower GI Restoration
NDC: 57955-0322 | Form: LIQUID
Manufacturer: King Bio Inc.
Category: homeopathic | Type: HUMAN OTC DRUG LABEL
Date: 20160408

ACTIVE INGREDIENTS: AETHUSA CYNAPIUM 10 [hp_X]/59 mL; GARLIC 10 [hp_X]/59 mL; BAPTISIA TINCTORIA ROOT 10 [hp_X]/59 mL; CAPSICUM 10 [hp_X]/59 mL; ACTIVATED CHARCOAL 10 [hp_X]/59 mL; MATRICARIA RECUTITA 10 [hp_X]/59 mL; CINCHONA OFFICINALIS BARK 10 [hp_X]/59 mL; COLLINSONIA CANADENSIS ROOT 10 [hp_X]/59 mL; CITRULLUS COLOCYNTHIS FRUIT PULP 10 [hp_X]/59 mL; MARSDENIA CONDURANGO BARK 10 [hp_X]/59 mL; GAMBOGE 10 [hp_X]/59 mL; GRATIOLA OFFICINALIS 10 [hp_X]/59 mL; COW MILK 10 [hp_X]/59 mL; LACTIC ACID, DL- 10 [hp_X]/59 mL; SODIUM CARBONATE 10 [hp_X]/59 mL; STRYCHNOS NUX-VOMICA SEED 10 [hp_X]/59 mL; PODOPHYLLUM 10 [hp_X]/59 mL; SEPIA OFFICINALIS JUICE 10 [hp_X]/59 mL; SILICON DIOXIDE 10 [hp_X]/59 mL
INACTIVE INGREDIENTS: WATER; ANHYDROUS CITRIC ACID; POTASSIUM SORBATE

Lower GI Restoration™

ACTIVE INGREDIENT

Drug Facts__________________________________________________________________________________________________________

HPUS active ingredients: Aethusa cynapium, Allium sativum, Baptisia tinctoria, Capsicum annuum, Carbo vegetabilis, Chamomilla, Cinchona officinalis, Collinsonia canadensis, Colocynthis, Condurango, Gambogia, Gratiola officinalis, Lac vaccinum, Lacticum acidum, Natrum carbonicum, Nux vomica, Podophyllum peltaum, Sepia, Silicea. Equal volumes of each ingredient in 10X, 30X, 100X, 1M, LM1, LM2, LM3 potencies.

INDICATIONS AND USAGE

Uses for temporary relief of symptoms of lower gastrointestinal distress: gas bloating, constipation, hemorrhoids, abdominal cramping, diarrhea, flatulence, gastrointestinal inflammation.

Inactive Ingredients:

Bio-Energetically Enhanced™ pure water, citric acid and potassium sorbate.

Warnings

- Stop use and ask your doctor if symptoms persist or worsen.
- If pregnant or breast-feeding, take only on advice of a healthcare professional.

- Keep out of reach of children.

Directions

- Initially, depress pump until primed.
- Spray one dose directly into mouth.
- Adults 12 and up: 3 sprays 3 times per day.
- Children 2-12 years: 2 sprays 3 times per day.
- Use additionally as needed, up to 6 times per day.

OTHER SAFETY INFORMATION

Tamper resistant for your protection. Use only if safety seal is intact. This product has not been clinically tested.

PURPOSE

Uses for temporary relief of symptoms of lower gastrointestinal distress:

- gas bloating
- constipation
- hemorrhoids
- abdominal cramping
- diarrhea
- flatulence
- gastrointestinal inflammation